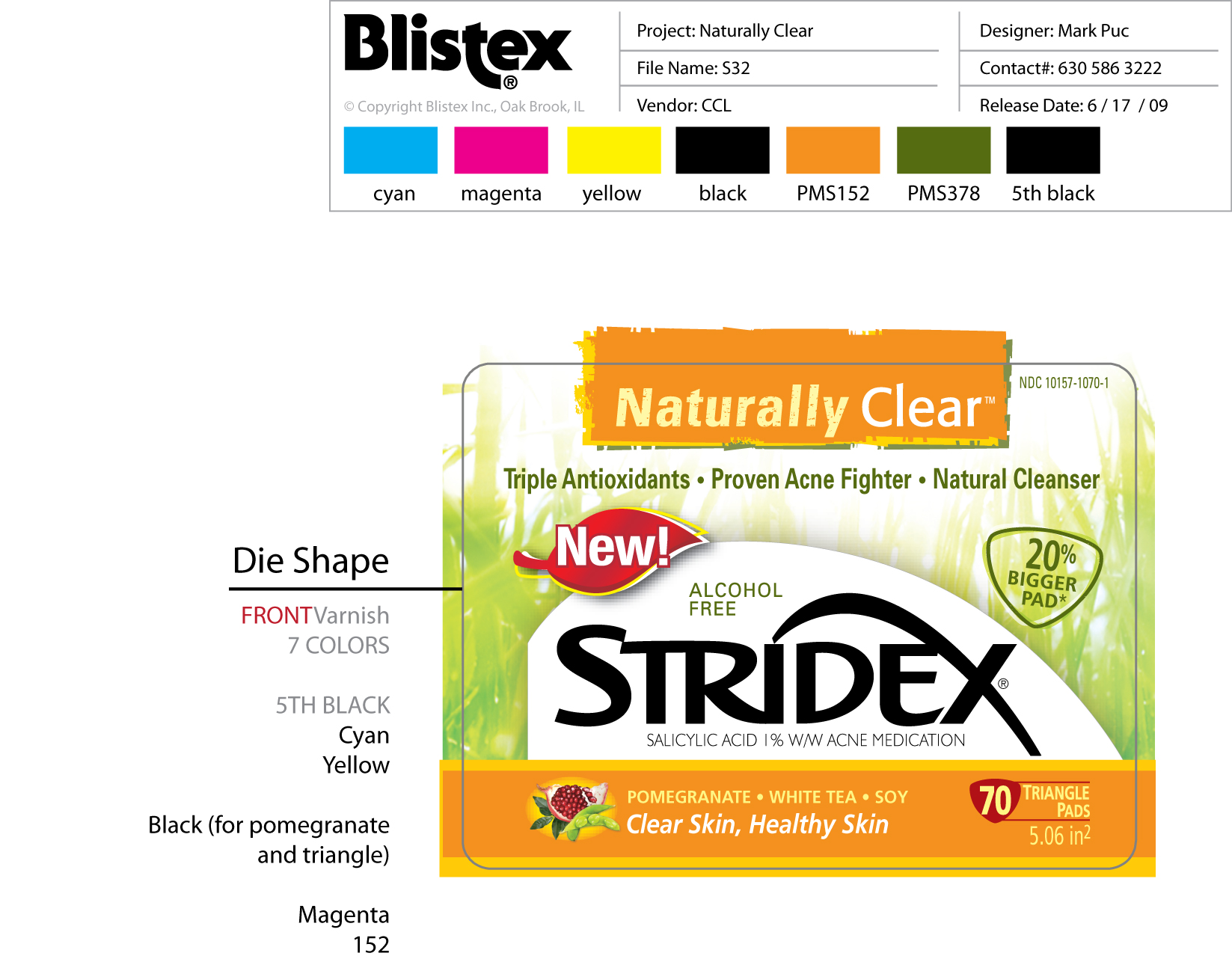 DRUG LABEL: STRIDEX
NDC: 10157-1070 | Form: LIQUID
Manufacturer: Blistex inc 
Category: otc | Type: HUMAN OTC DRUG LABEL
Date: 20091123

ACTIVE INGREDIENTS: SALICYLIC ACID 0.1 g/1 1

DRUG FACTS

ACTIVE INGREDIENT

SALICYLIC ACID 1% WITH ACNE MEDICATION

PURPOSE

Acne medication

- For the treatment and management of acne
- reduces the number of acne pimples and blackheads and allows the skin to heal
- helps to prevent new acne pimples from forming

WHEN USING

FOR EXTERNAL USE ONLY

Allergy alert:

do not use this product it you have a known allergy to salicylic acid.

- Cleanse the skin thoroughly before applying medication
- use the pad to wipe the entire affected area
- repeat with a clean pad as necessary to remove remaining traces of dirt,because excessive drying of the skin may occur , start with one application

daily , then gradually increase to two to three times daily as needed or as directed by a doctor

- if bothersome dryness or peeling occurs, reduce application to once a day or every other day
- do not leave pad on skin for an extended period of time
- keep away from eyes ,lips and other mucous membrane

using other topical acne medications at the same time or immediately following use of this product may increase
dryness or irritation of the skin. If this occurs , only one medication should be used unless directed by doctor.

KEEP OUT OF REACH OF CHILDREN

If swallowed get get medical help or contact a posion control center right away.

PACKAGE LABEL

Naturally Clear
Stridex
The Natural acne solution with the proven effectiveness of stridex